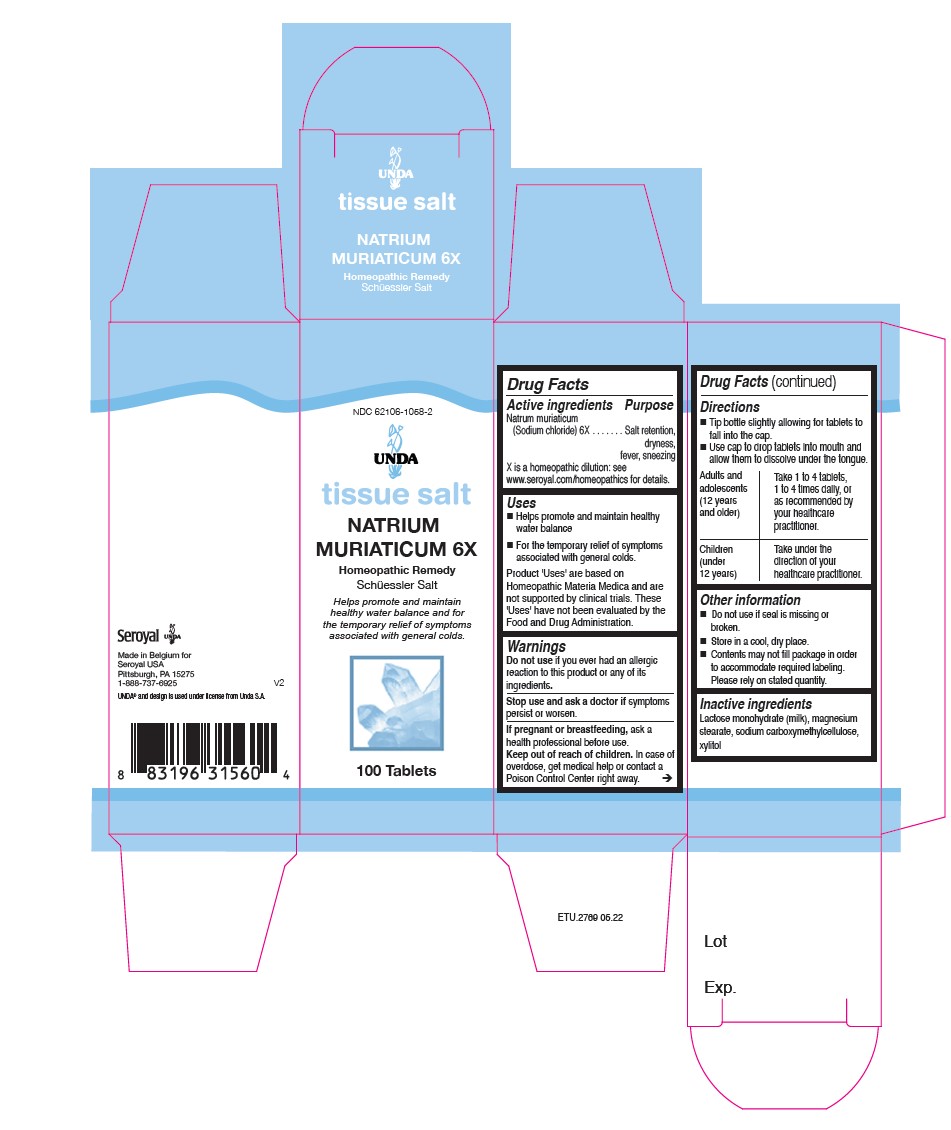 DRUG LABEL: Natrium Muriaticum 6X
NDC: 62106-1058 | Form: TABLET
Manufacturer: Seroyal USA
Category: homeopathic | Type: HUMAN OTC DRUG LABEL
Date: 20220707

ACTIVE INGREDIENTS: SODIUM CHLORIDE 6 [hp_X]/1 1
INACTIVE INGREDIENTS: LACTOSE MONOHYDRATE; XYLITOL; CARBOXYMETHYLCELLULOSE SODIUM; MAGNESIUM STEARATE

Natrium Muriaticum 6X

Active Ingredients

Natrum muriaticum (Sodium chloride) 6X

Uses

Helps promote and maintain healthy water balance.

For the temporary relief of symptoms associated with general colds.

Warnings

Do not use if you ever had an allergic reaction to this product or any of its ingredients.

Stop use and ask a doctor if symptoms persist or worsen.

If you are pregnant or breastfeeding, ask a healthcare practitioner before use.
Keep out of reach of children.

In case of overdose, get medical help or contact
a Poison Control Center right away.

PREGNANCY OR BREAST FEEDING

If you are pregnant or breastfeeding, ask a healthcare practitioner before use.

Keep out of reach of children.

OVERDOSAGE

In case of overdose, get medical help or contact

a Poison Control Center right away.

Stop use and ask a doctor if symptoms persist or worsen.

Inactive Ingredients

Lactose monohydrate (milk), magnesium stearate, sodium carboxymethylcellulose, xylitol

Directions

Tip bottle slightly allowing for tablets to
fall into the cap.
Use cap to drop tablets into mouth and
allow them to dissolve under the tongue.

Adults and adolescents (12 years and older): Take 1 to 4 tablets, one to four times daily,

or as recommended by your healthcare practitioner.

Children (under 12 years): Take under the direction of your healthcare practitioner.

Uses

Helps promote and maintain healthy water balance.

For the temporary relief of symptoms associated with general colds.

Directions

Tip bottle slightly allowing tablets to fall into cap.

Use cap to drop tablets into mouth and allow them to dissolve under the tongue.
Adults and adolescents (12 years and older): Take 1 to 4 tablets, one to
four times daily, or as recommended by your healthcare practitioner.

Children (under 12 years): Take under the direction of your healthcare practitioner.

Other information

Do not use if seal is missing or broken.

Store in a cool, dry place.

PACKAGE LABEL

NDC 62106-1058-2

UNDA

tissue salt

NATRIUM MURIATICUM 6X

Homeopathic Preparation

Schüessler Salt

Helps promote and maintain healthy water balance and for the temporary relief of symptoms associated with general colds.

100 Tablets